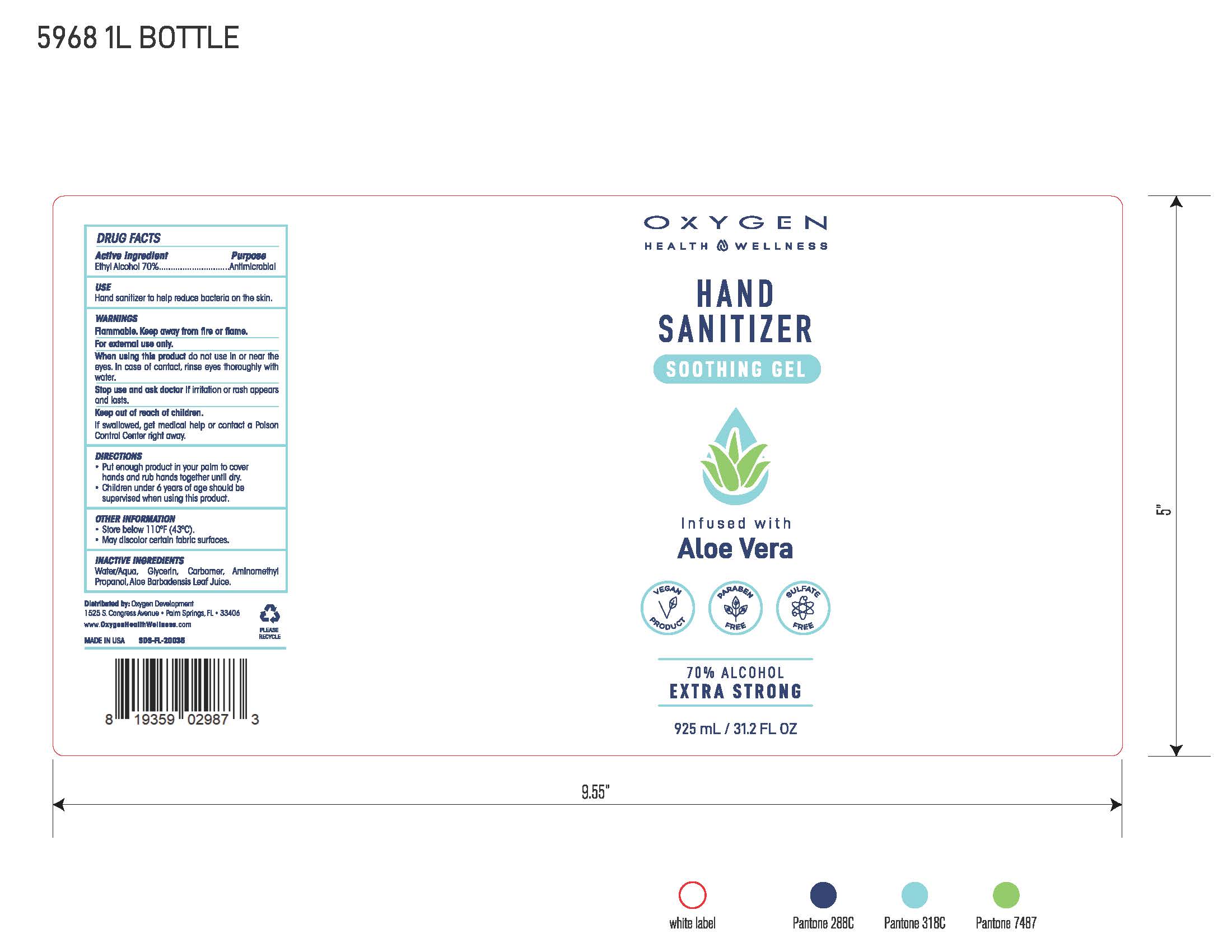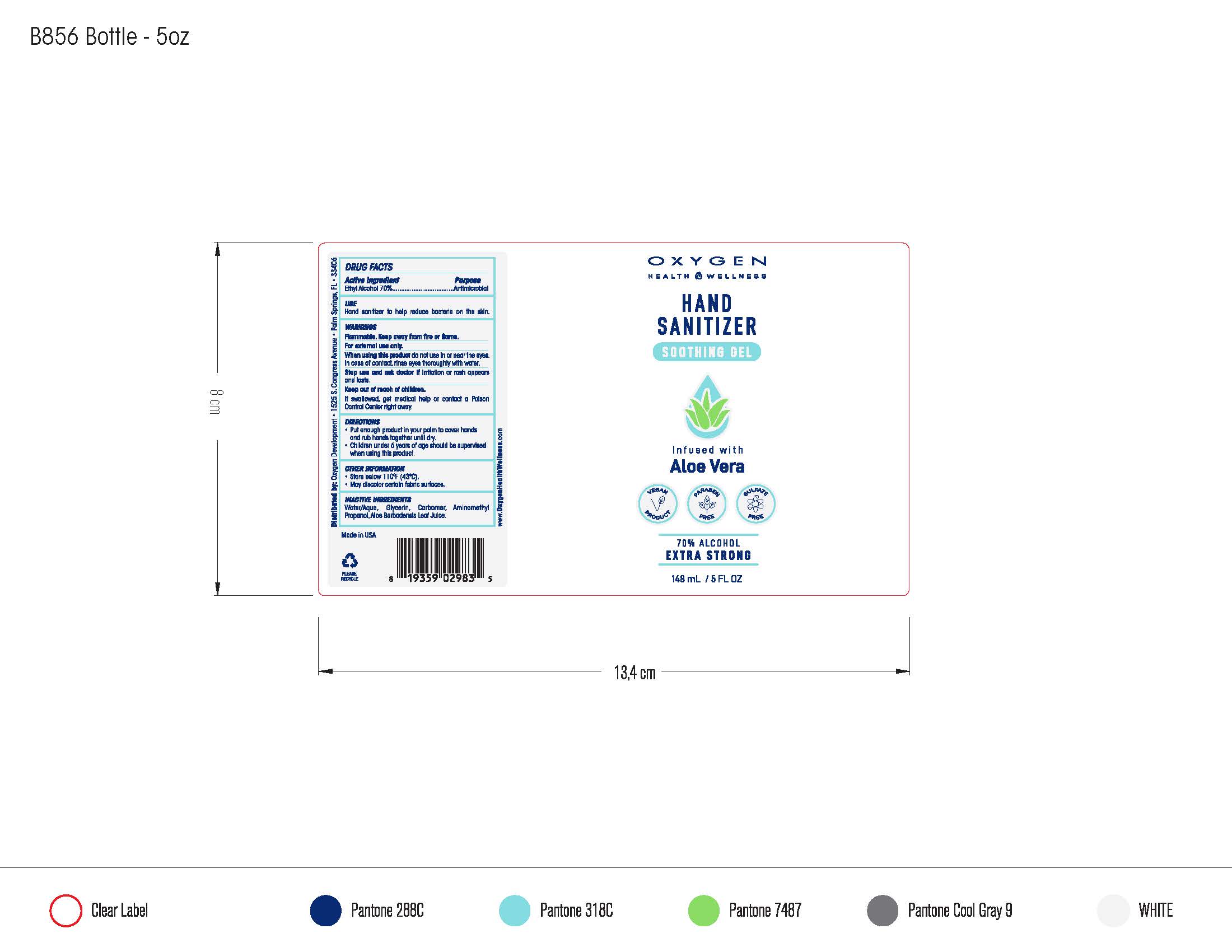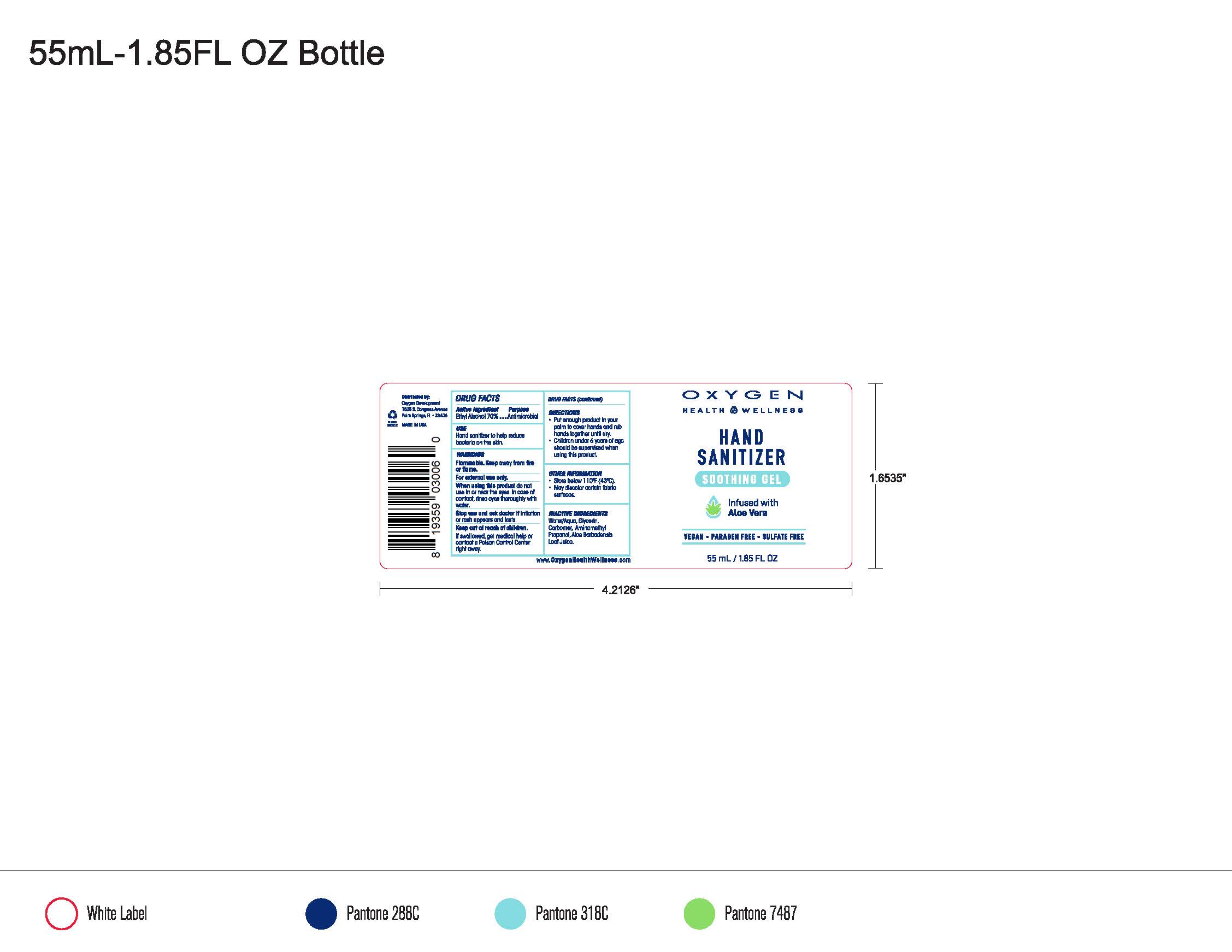 DRUG LABEL: Hand Sanitizer Soothing Gel
NDC: 61354-010 | Form: LIQUID
Manufacturer: OXYGEN DEVELOPMENT, LLC
Category: otc | Type: HUMAN OTC DRUG LABEL
Date: 20200608

ACTIVE INGREDIENTS: ALCOHOL 70.473 mL/100 mL
INACTIVE INGREDIENTS: GLYCERIN 1.496 mL/100 mL; CARBOMER 940 0.5 mL/100 mL; WATER 27.445 mL/100 mL

OXYGEN HEALTH & WELLNESS HAND SANITIZER SOOTHING GEL INFUSED WITH ALOE VERA

Active Ingredient(s)

Ethyl Alcohol 70% v/v. Purpose: Antimicrobial

Purpose

Antimicrobial, Hand Sanitizer

Use

Hand Sanitizer to help reduce bacteria on the skin.

Warnings

Flammable. Keep away from heat or flame. For external use only

When using this product do not use in or near the eyes. In case of contact, rinse eyes thoroughly with water.

Stop use and ask a doctor if irritation or rash appears and lasts.

Keep out of reach of children. If swallowed, get medical help or contact a Poison Control Center right away.

Directions

- Place enough product in your palm to cover hands and rub hands together until dry.
- Children under 6 years of age should be supervised when using this product.

Other information

- Store below 110F (43C).
- May discolor certain fabric surfaces.

Inactive ingredients

Water/Aqua,Glycerin, Carbomer, Aminomethyl Propanol, Aloe Barbadensis Leaf Juice.

Package Label - Principal Display Panel

925 mL NDC: 61354-010-01

Package Label- Principal Display Panel

148 mL NDC:61354-010-02

Package Label- Principal Display Panel

55 mL NDC:61354-010-03